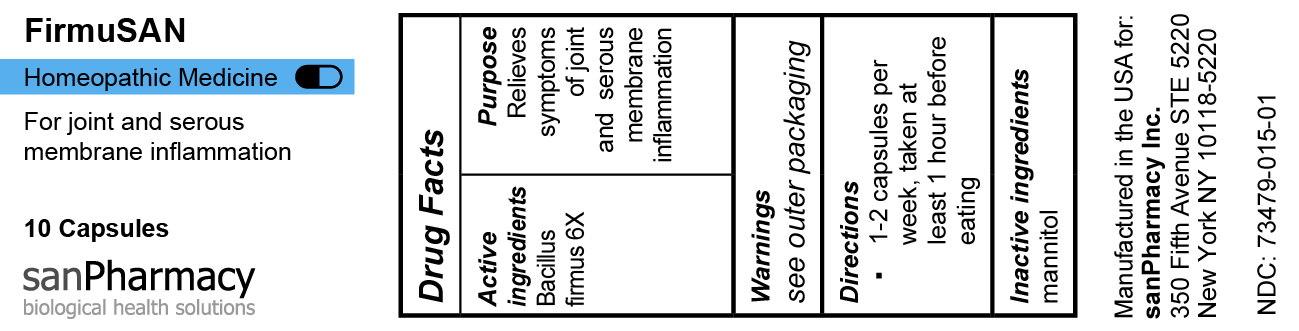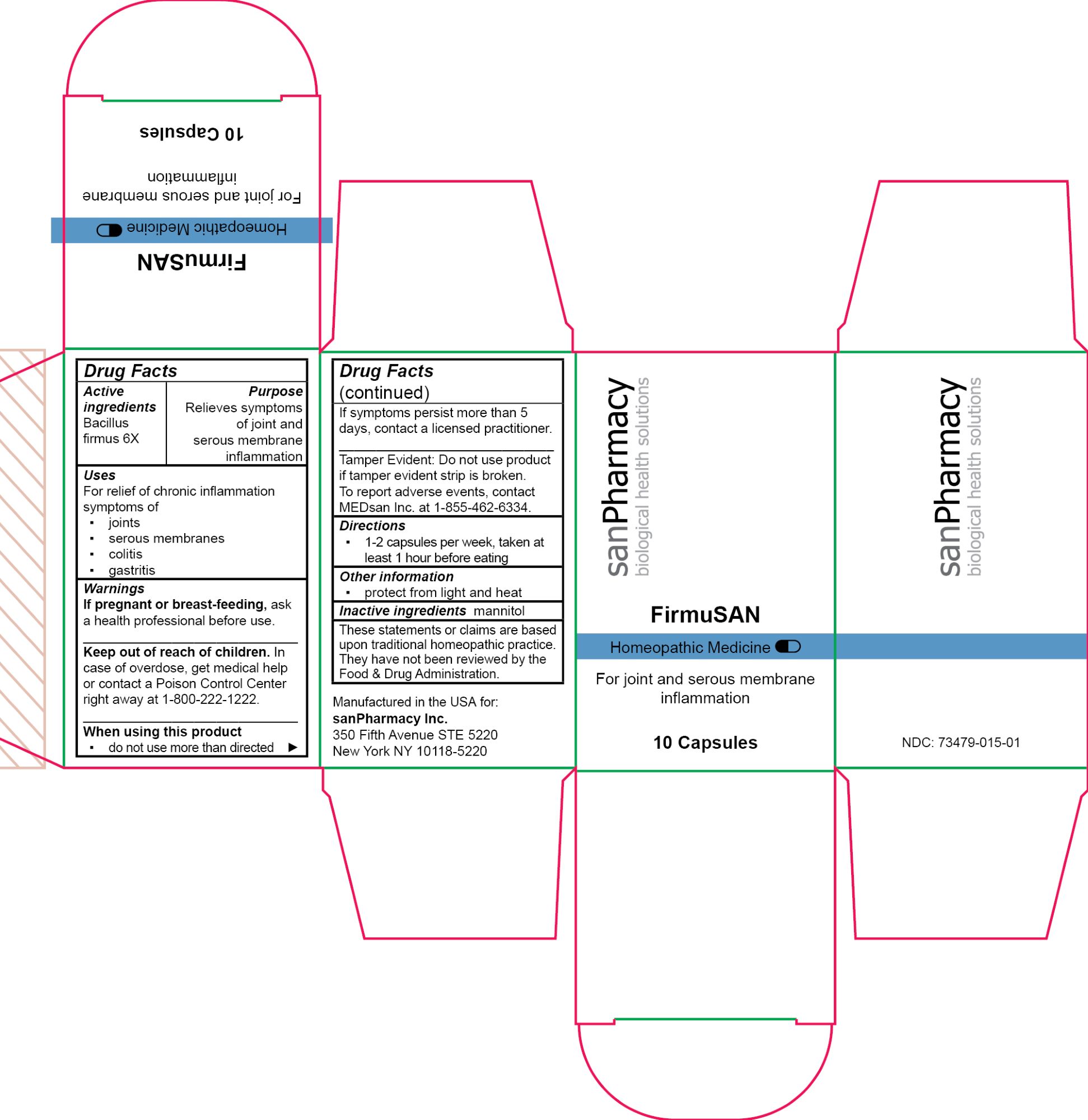 DRUG LABEL: FirmuSAN
NDC: 73479-015 | Form: CAPSULE
Manufacturer: sanPharmacy Inc.
Category: homeopathic | Type: HUMAN OTC DRUG LABEL
Date: 20240429

ACTIVE INGREDIENTS: BACILLUS FIRMUS 6 [hp_X]/1 1
INACTIVE INGREDIENTS: MANNITOL

FirmuSAN Capsules

Indications

For joint and serous membrane inflammation

Purpose

Relieves symptoms of joint and serous membrane inflammation

Dosage

1-2 capsules per week, taken at least 1 hour before eating

Active ingredients

Bacillus firmus 6X

Inactive ingeredients

mannitol

Warnings

If pregnant or breast-feeding, ask a health professional before use.
______________________________
Keep out of reach of children. In case of overdose, get medical help or contact a Poison Control Center right away at 1-800-222-1222.
______________________________
When using this product
▪ do not use more than directed
______________________________
If symptoms persist more than 5 days, contact a licensed practitioner.
______________________________
Tamper Evident: Do not use product if tamper evident strip is broken. To report adverse events, contact MEDsan Inc. at 1-855-462-6334.

Keep out of reach of children. In case of overdose, get medical help or contact a Poison Control Center right away at 1-800-222-1222

Manufactured in the USA for:
sanPharmacy Inc.
350 Fifth Avenue STE 5220
New York NY 10118-5220

Liability statement

These statements or claims are based upon traditional homeopathic practice. They have not been reviewed by the Food & Drug Administration

STORAGE AND HANDLING

protect from light and heat

PACKAGE LABEL

FirmuSAN

Homeopathic Medicine

For joint and serous membrane inflammation

10 Capsules

sanPharmacy

biological health solutions